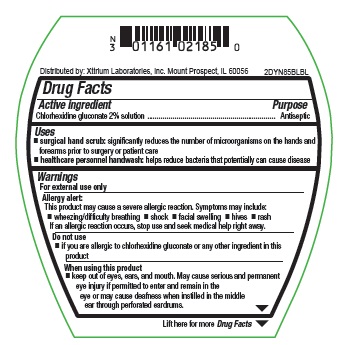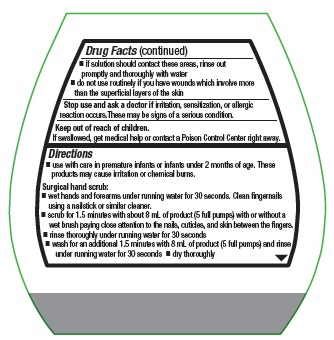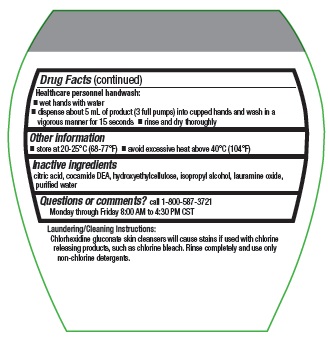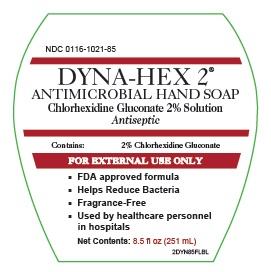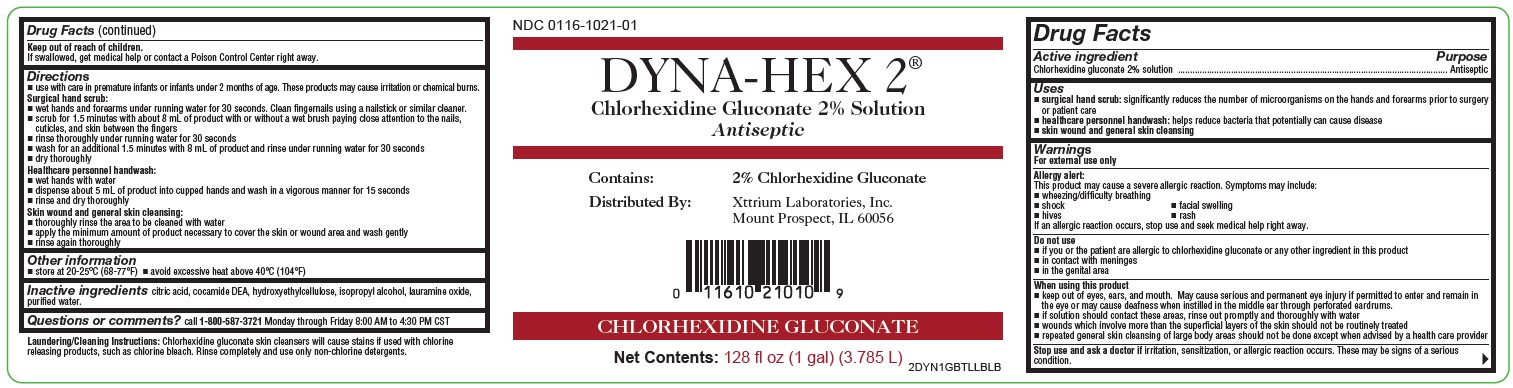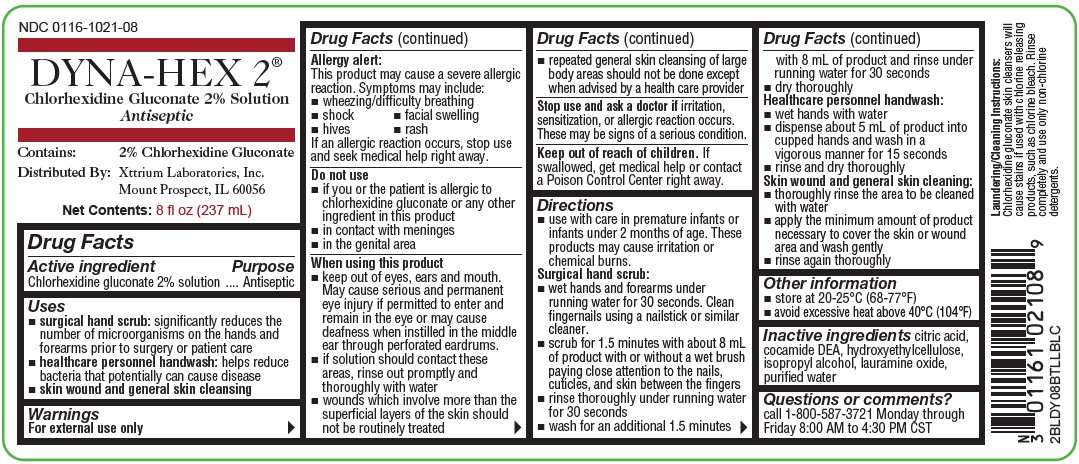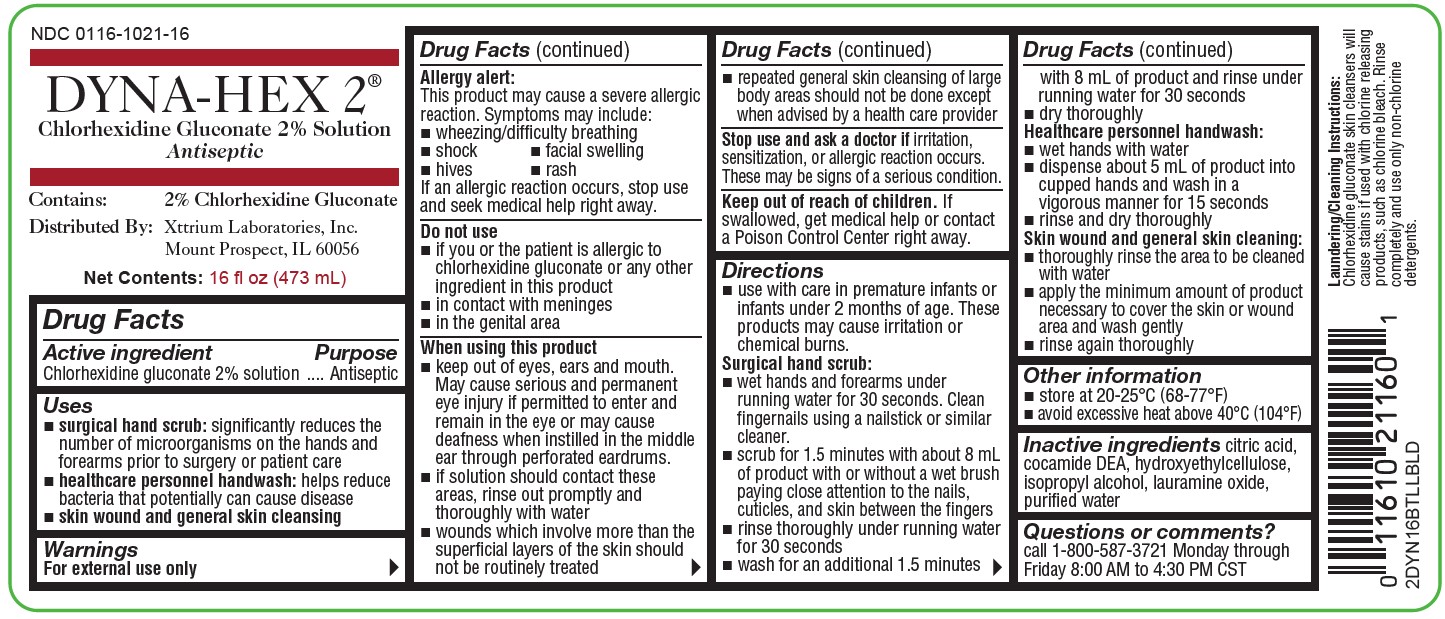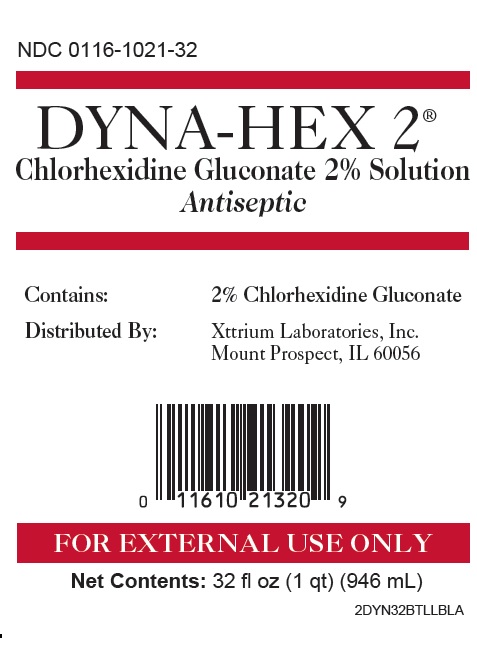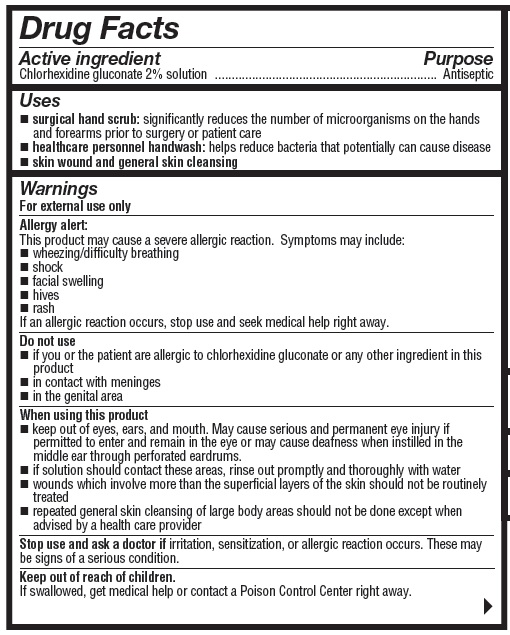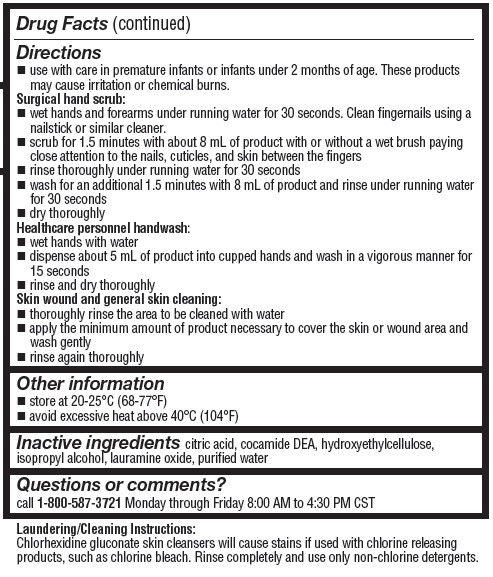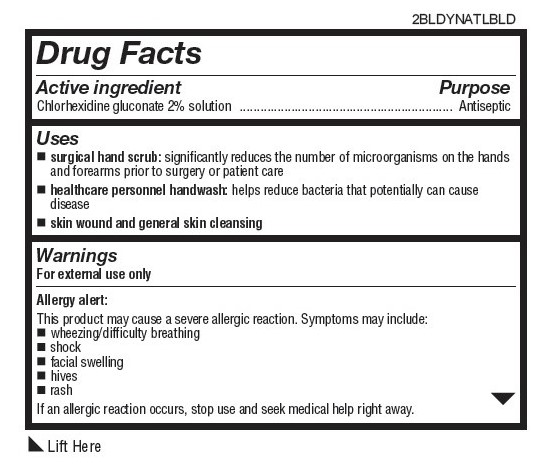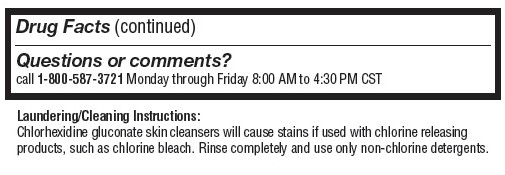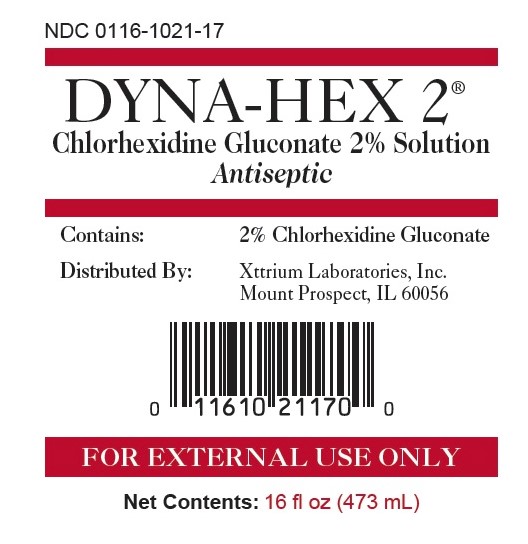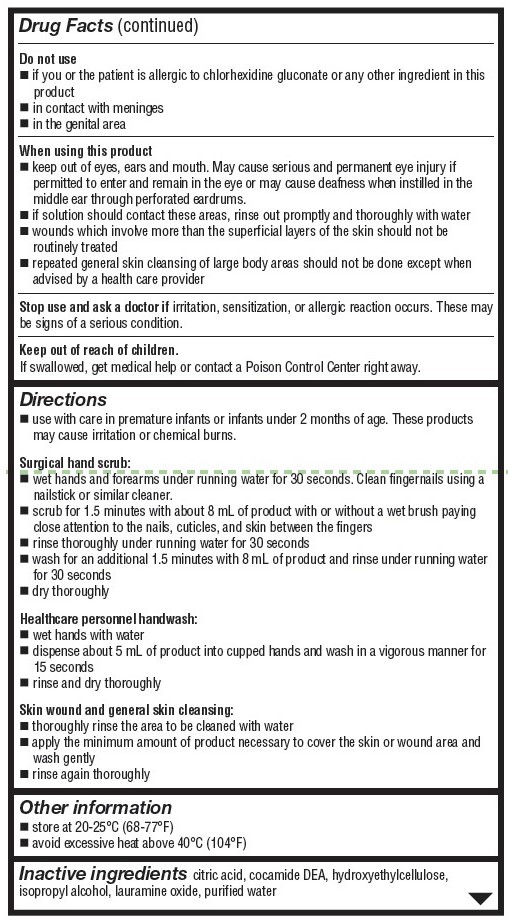 DRUG LABEL: DYNA-HEX
NDC: 0116-1021 | Form: LIQUID
Manufacturer: Xttrium Laboratories, Inc.
Category: otc | Type: HUMAN OTC DRUG LABEL
Date: 20251210

ACTIVE INGREDIENTS: CHLORHEXIDINE GLUCONATE 2 g/100 mL
INACTIVE INGREDIENTS: CITRIC ACID MONOHYDRATE; COCO DIETHANOLAMIDE; HYDROXYETHYL CELLULOSE (2000 MPA.S AT 1%); ISOPROPYL ALCOHOL; LAURAMINE OXIDE; WATER

Dyna-Hex 2: 8.5oz, 16oz (other)
COMP 8oz, 16oz, 32oz, 1GL

Drug Facts

Active ingredient

chlorhexidine gluconate 2% solution

Purpose

Antiseptic

Uses

- surgical hand scrub: significantly reduces the number of microorganisms on the hands and forearms prior to surgery or patient care
- healthcare personnel handwash: helps reduce bacteria that potentially can cause disease
- skin wound and general skin cleansing

Warnings

For external use only

Allergy alert:

This product may cause a severe allergic reaction. Symptoms may include: wheezing/difficulty breathing
shock

facial swelling
hives
rash
If an allergic reaction occurs, stop use and seek medical help right away.

Do not use

- if you or the patient is allergic to chlorhexidine gluconate or any other ingredient in this product
- in contact with meninges
- in the genital area

When using this product

- keep out of eyes, ears and mouth. May cause serious and permanent eye injury if permitted to enter and remain in the eye or may cause deafness when instilled in the middle ear through perforated eardrums.
- if solution should contact these areas, rinse out promptly and thoroughly with water
- wounds that involve more than the superficial layers of the skin should not be routinely treated
- repeated general skin cleansing of large body areas should not be done except when advised by a health care provider

Stop use and ask a doctor if irritation, sensitization, or allergic reaction occurs. These may be signs of a serious condition.

Keep out of reach of children. If swallowed, get medical help or contact a Poison Control Center right away.

Stop use and ask a doctor if

irritation, sensitization, or allergic reaction occurs. These may be signs of a serious condition.

Keep out of reach of children

If swallowed, get medical help or contact a Poison Control Center right away.

Directions

- Use with care in premature infants or infants under 2 months of age. These products may cause irritation or chemical burns.

Surgical hand scrub:

wet hands and forearms under running water for 30 seconds. Clean fingernails using a nailstick or similar cleaner.

scrub for 1.5 minutes with about 8 mL of product with or without a wet brush paying close attention to the nails, cuticles, and skin between the fingers

rinse thoroughly under running water for 30 seconds

wash for an additional 1.5 minutes with 8 mL of product and rinse under running water for 30 seconds

dry thoroughly

Healthcare personnel handwash:
wet hands with water
dispense about 5 mL of product into cupped hands and wash in a vigorous manner for 15 seconds

rinse and dry thoroughly

Skin wound and general skin cleaning:

thoroughly rinse the area to be cleaned with water

apply the minimum amount of product necessary to cover the skin or wound area and wash gently

rinse again thoroughly

Other information

- store at 20-25° C (68-77° F)
- avoid excessive heat above 40° C (104° F)

Inactive ingredients

citric add. cocamide DEA, hydroxyethylcellulose, isopropyl alcohol, lauramine oxide, purified water

Questions or comments?

call 1-800-587-3721
Monday through Friday 8:00 AM to 4:30 PM CST

PACKAGE LABEL

DYNA-HEX 2®

NDC 0116-1021-08

Chlorhexidine Gluconate 2% Solution

Antiseptic Foam Handwash

Distributed by:

Xttrium Laboratories, Inc.

Mount Prospect, IL 60056

2BLDY08BTLLBLC

Net Wt 8 fl oz (237 mL)

NDC 0116-1021-85

DYNA-HEX 2®ANTIMICROBIAL HAND SOAP

Chlorhexidine Gluconate 2% Solution

Antiseptic

Contains: 2% Chlorhxidine Gluconate

FOR EXTERNAL USE ONLY

FDA approved formula

Helps Reduce Bacteria

Fragrance-Free

Used by Healthcare personnel in hospitals

Net Contents: 8.5 fl oz (251 mL)

2DYN85FLBL

NDC 0116-1021-16

Dyna-Hex 2 ®

Chlorhexidine Gluconate 2% Solution

Antiseptic Foam Handwash

Distributed by:

Xttrium Laboratories, Inc.

Mount Prospect, IL 60056

2DYN16BTLLBLD

Net Wt 16 fl oz (473 mL)

NDC 0116-1021-17

Dyna-Hex 2®

Chlorhexidine Gluconate 2% Solution

Antiseptic Foam Handwash

Distributed by:

Xttrium Laboratories, Inc.

Mount Prospect, IL 60056

2BLDYNATLBLD

Net Wt 16 fl oz (473 mL)

NDC 0116-1021-32

Dyna-Hex 2®

Chlorhexidine Gluconate 2% Solution

Antiseptic Foam Handwash

Distributed by:

Xttrium Laboratories, Inc.

Mount Prospect, IL 60056

2DYN32BTLLBLA

Net Wt 32 fl oz (946 mL)

NDC 0116-1021-01

Dyna-Hex 2®

Chlorhexidine Gluconate 2% Solution

Antiseptic Foam Handwash

Distributed by:

Xttrium Laboratories, Inc.

Mount Prospect, IL 60056

2DYN1GBTLLBLB

Net Wt 128 fl oz (1 gal)